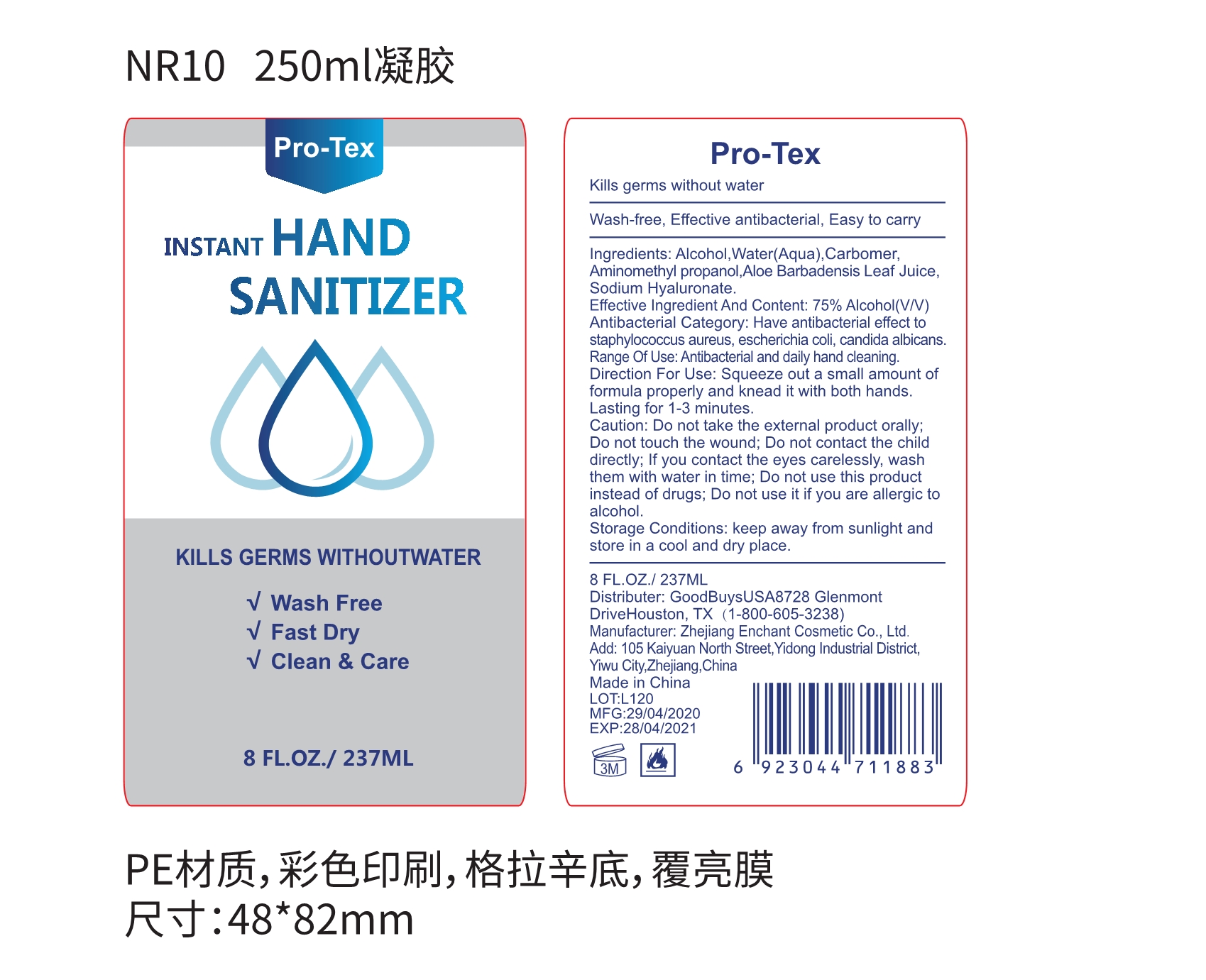 DRUG LABEL: Pro-Tex  HAND SANITIZER
NDC: 52728-020 | Form: GEL
Manufacturer: Zhejiang Enchant Cosmetic Co., Ltd.
Category: otc | Type: HUMAN OTC DRUG LABEL
Date: 20200710

ACTIVE INGREDIENTS: ALCOHOL 177.75 mL/237 mL
INACTIVE INGREDIENTS: POLYACRYLIC ACID (250000 MW) 0.948 mL/237 mL; AMINOMETHYLPROPANOL 0.711 mL/237 mL; WATER 57.354 mL/237 mL; ALOE VERA LEAF 0.2133 mL/237 mL; HYALURONATE SODIUM 0.0237 mL/237 mL

Zhejiang Enchant Cosmetic Co., Ltd.
52728-020-01
GOODBUYS USA INC

Active Ingredient(s)

75% Alcohol(V/V).

Purpose

Antibacterial and dialy hand cleaning.

Have antibacterial effect to staphylococcus aureus, escherichia coli, candida albicans.

Use

Squeeze out a small amount of formula properly and knead it with both hands.
Lasting for 1-3 minutes.

Warnings

Do not take the external product orally;
Do not touch the wound;
Do not contact the child directly;
If you contact the eyes carelessly, wash them with water in time;
Do not use this product instead of drugs;
Do not use it if you are allergic to alcohol.

Keep out of reach of children. If swallowed, get medical help or contact a Poison Control Center right away.

DOSAGE AND ADMINISTRATION

Place enough product on hands to cover all surfaces. Rub hands together until dry.
Supervise children under 6 years of age when using this product to avoid swallowing.

Other information

Keep away from sunlight and store in a cool and dry place.

Inactive ingredients

Water(Aqua), Carbomer, Aminomethyl propanol, Aloe Barbadensis Leaf Juice, Sodium Hyaluronate.

Package Label - Principal Display Panel

237 mL in 1 BOTTLE NDC: 52728-020-01